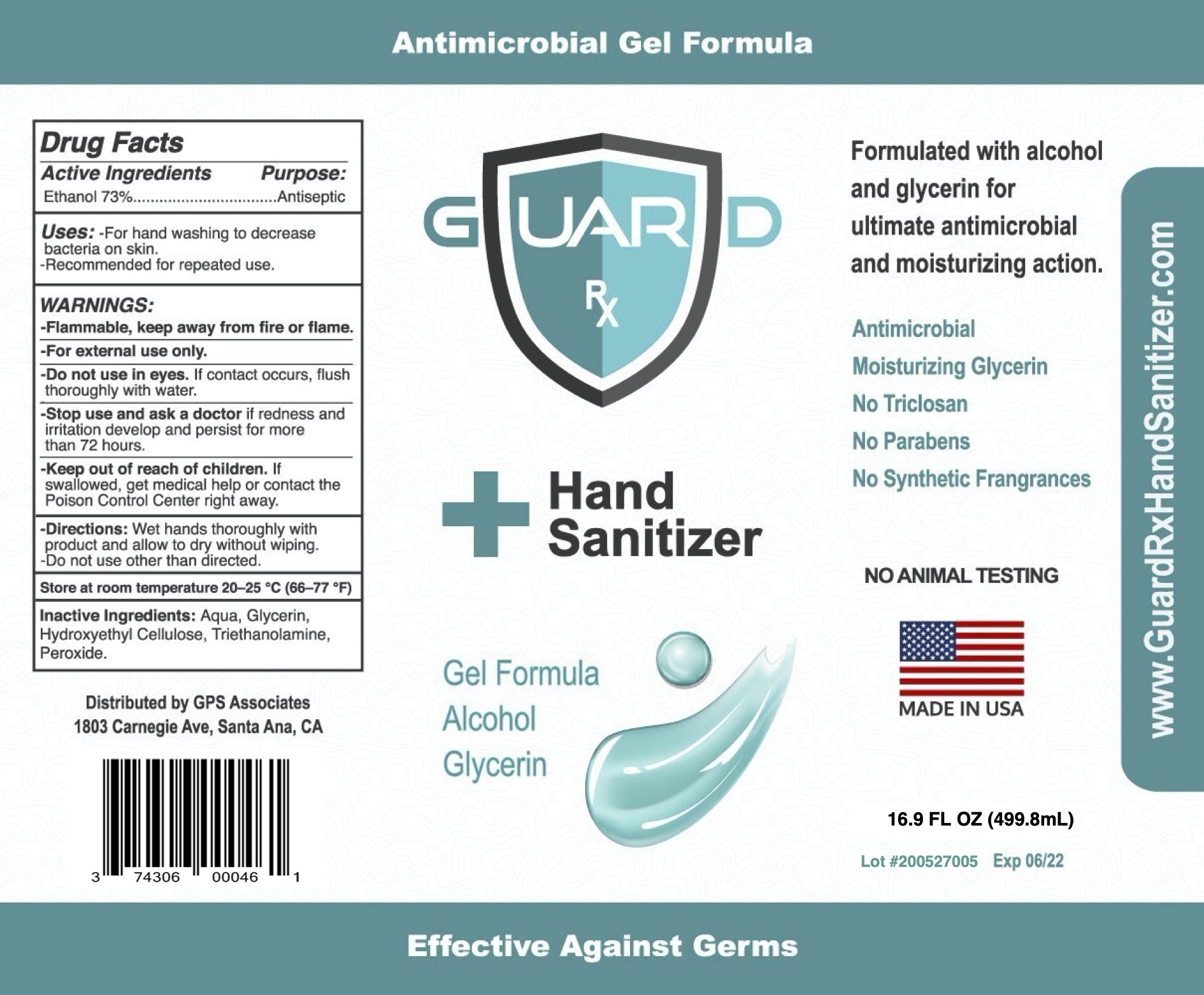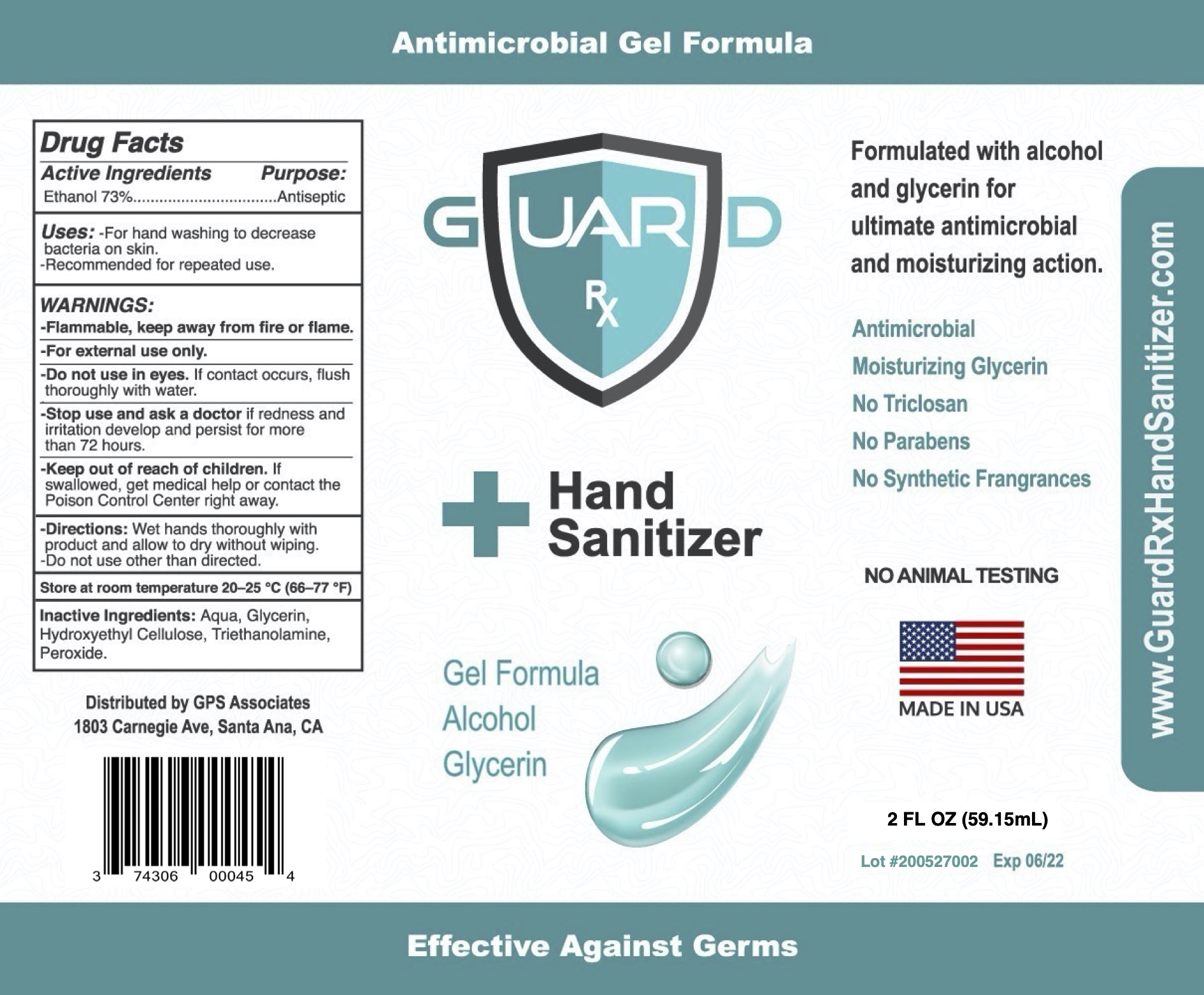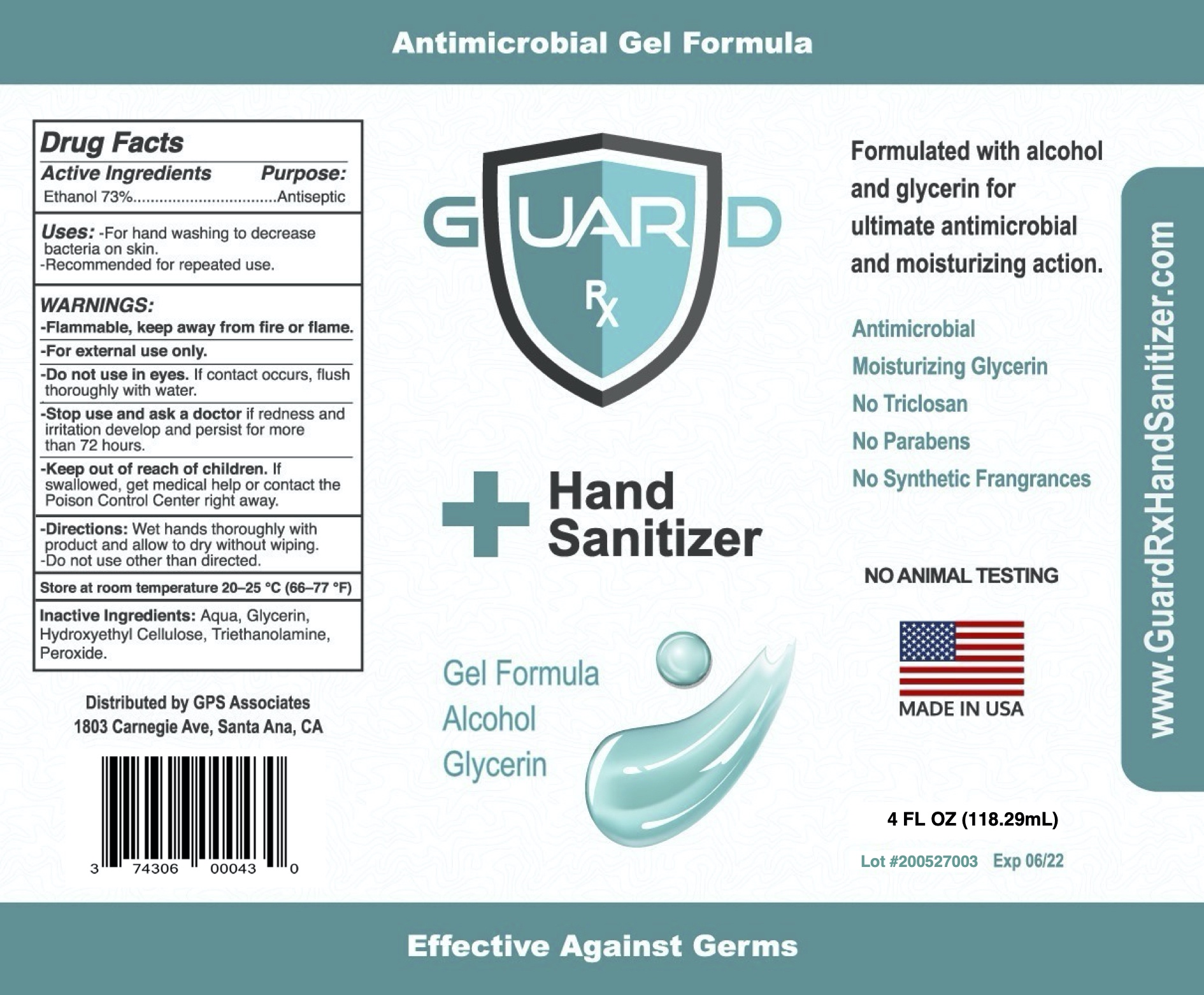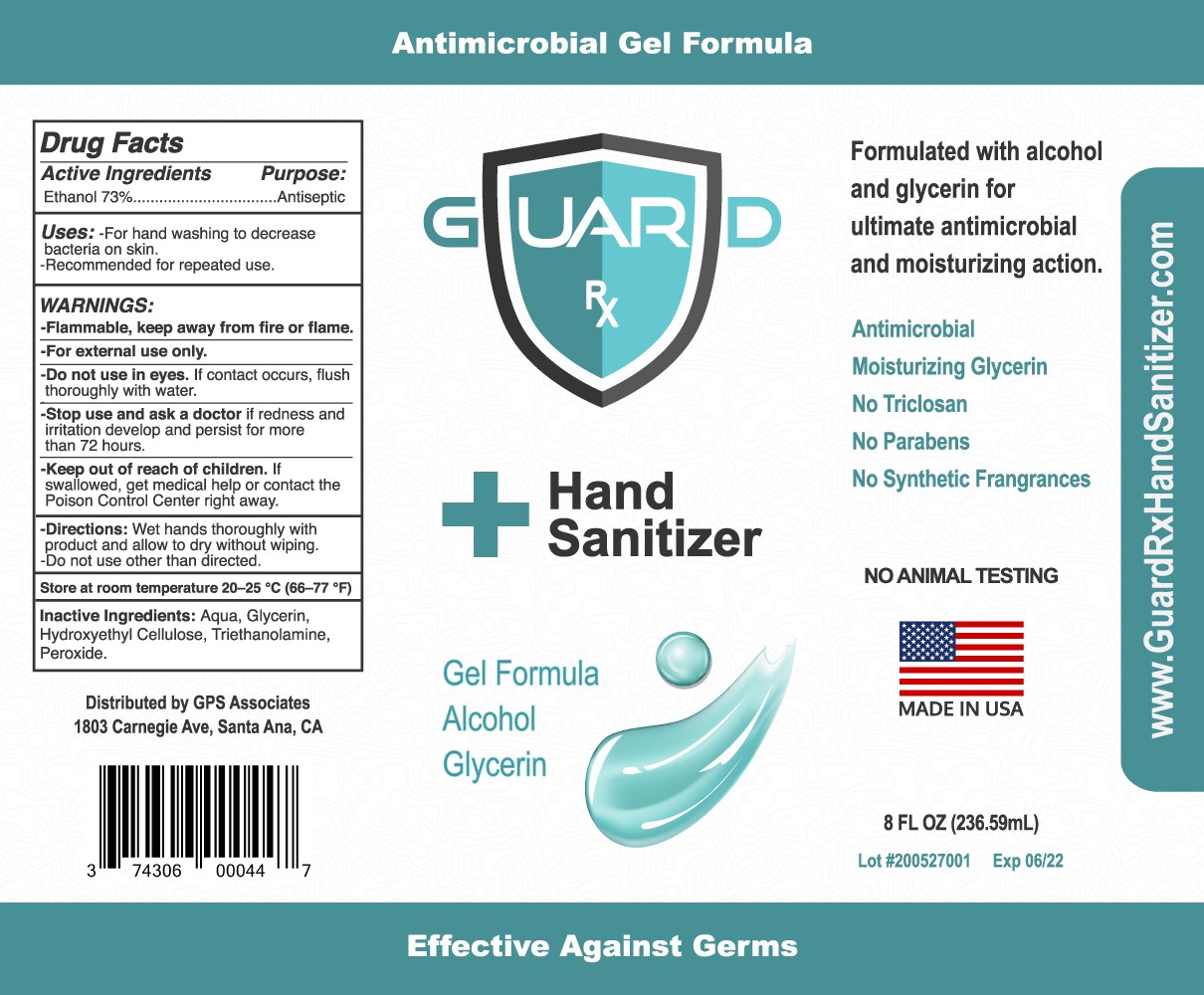 DRUG LABEL: GuardRx Gel Hand Sanitizer
NDC: 74306-234 | Form: GEL
Manufacturer: GPS Associates
Category: otc | Type: HUMAN OTC DRUG LABEL
Date: 20200521

ACTIVE INGREDIENTS: ALCOHOL 73 mL/100 mL
INACTIVE INGREDIENTS: TRIETHANOLAMINE LACTATE; WATER; HYDROGEN PEROXIDE; HYDROXYPROPYL CELLULOSE, UNSPECIFIED; GLYCERIN

ACTIVE INGREDIENT

Ethanol 73%

Purpose:

Antiseptic

Uses:

-For hand washing to decrease bacteria on skin.

-Recommended for repeated use.

WARNINGS:

-Flammable, keep away from fire or flame.

WHEN USING

-For external use only.

-Do not use in eyes. If contact occurs, flush thoroughly with water.

-Stop use and ask doctor if redness and irritation develop and persist for more than 72 hours.

-Keep out of reach of children. If swallowed, get medical help or contact the Poison Control Center right away.

Directions:

Wet hands thoroughly with product and allow to dry without wiping.

-Do not use other than directed.

STORAGE AND HANDLING

Store at room temperature 20-25 °C (66-77 °F)

INACTIVE INGREDIENT

Aqua, Glycerin, Hydroxypropyl Cellulose, Triethanolamine, Hydrogen Peroxide,